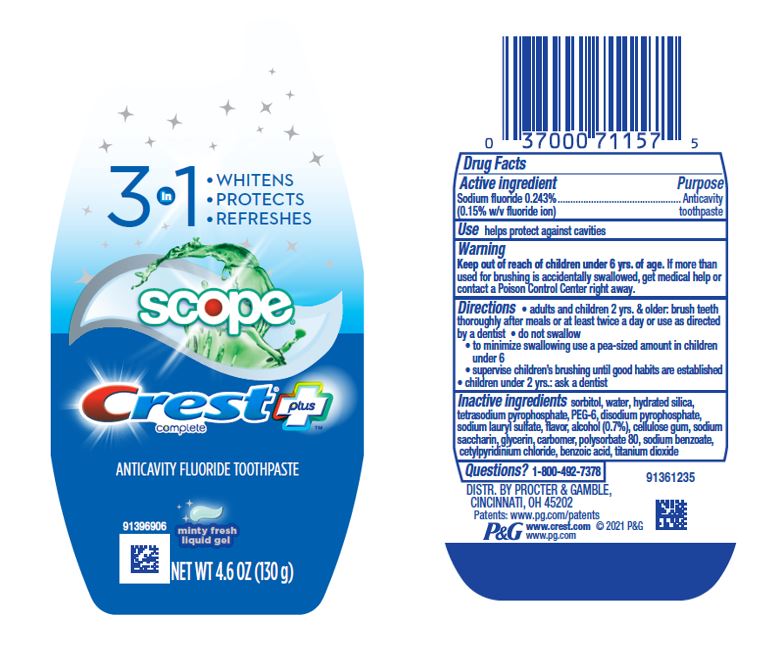 DRUG LABEL: Crest Complete Plus
NDC: 37000-984 | Form: GEL, DENTIFRICE
Manufacturer: The Procter & Gamble Manufacturing Company
Category: otc | Type: HUMAN OTC DRUG LABEL
Date: 20250225

ACTIVE INGREDIENTS: SODIUM FLUORIDE 1.5 mg/1 g
INACTIVE INGREDIENTS: SORBITOL; WATER; HYDRATED SILICA; POLYETHYLENE GLYCOL 300; SODIUM PYROPHOSPHATE; CARBOXYPOLYMETHYLENE; SODIUM LAURYL SULFATE; ALCOHOL; CARBOXYMETHYLCELLULOSE SODIUM; SACCHARIN SODIUM; GLYCERIN; POLYSORBATE 80; SODIUM BENZOATE; CETYLPYRIDINIUM CHLORIDE; SODIUM PHOSPHATE, DIBASIC, ANHYDROUS; TITANIUM DIOXIDE; BENZOIC ACID

Crest Complete Plus 3 in 1 Liquid Gel

Drug Facts

Active ingredient

Sodium fluoride 0.243%

(0.15% w/v fluoride ion)

Purpose

Anticavity toothpaste

Use

helps protect against cavities

Warnings

Keep out of reach of children under 6 yrs. of age. If more than used for brushing is accidentally swallowed, get medical help or contact a Poison Control Center right away.

Directions

- adults and children 2 yrs. & older: brush teeth thoroughly after meals or at least twice a day or use as directed by a dentist
  - do not swallow
  - to minimize swallowing use a pea-sized amount in children under 6
  - supervise children's brushing until good habits are established
- children under 2 yrs.: ask a dentist

Inactive ingredients

sorbitol, water, hydrated silica, tetrasodium pyrophosphate, PEG-6, disodium pyrophosphate, sodium lauryl sulfate, flavor, alcohol (0.7%), cellulose gum, sodium saccharin, glycerin, carbomer, polysorbate 80, sodium benzoate, cetylpyridinium chloride, benzoic acid, titanium dioxide

Questions?

1-800-492-7378

Dist. by Procter & Gamble, Cincinnati, OH 45202

PRINCIPAL DISPLAY PANEL - 130 g Bottle Label

3 in 1

WHITENS

PROTECTS

REFRESHES

scope®

Crest® plus
complete

ANTICAVITY FLUORIDE TOOTHPASTE
minty fresh liquid gel

NET WT 4.6 OZ (130 g)